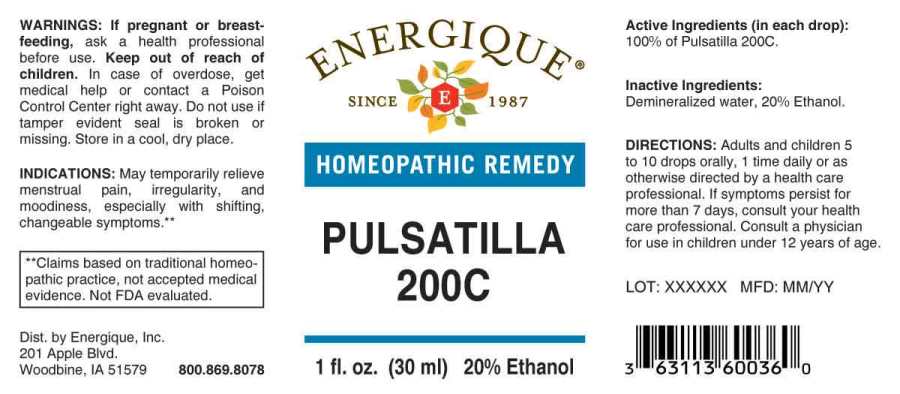 DRUG LABEL: Pulsatilla
NDC: 44911-0498 | Form: LIQUID
Manufacturer: Energique, Inc.
Category: homeopathic | Type: HUMAN OTC DRUG LABEL
Date: 20241029

ACTIVE INGREDIENTS: PULSATILLA PRATENSIS WHOLE 200 [hp_C]/1 mL
INACTIVE INGREDIENTS: WATER; ALCOHOL

DRUG FACTS:

ACTIVE INGREDIENT:

(in each drop): 100% of Pulsatilla (Pratensis) 200C.

INDICATIONS:

May temporarily relieve menstrual pain, irregularity, and moodiness, especially with shifting, changeable symptoms.

WARNINGS:

If pregnant or breastfeeding, ask a health professional before use.

Keep out of reach of children. In case of overdose, get medical help or contact a Poison Control Center right away.

Do not use if tamper evident seal is broken or missing.

Store in a cool, dry place.

Keep out of reach of children. In case of overdose, get medical help or contact a Poison Control Center right away.

DIRECTIONS:

Adults and children 5 to 10 drops orally, 1 time daily or as otherwise directed by a health care professional. If symptoms persist for more than 7 days, consult your health care professional. Consult a physician for use in children under 12 years of age.

INDICATIONS:

May temporarily relieve menstrual pain, irregularity, and moodiness, especially with shifting, changeable symptoms.

INACTIVE INGREDIENTS:

Demineralized water, 20% Ethanol

QUESTIONS:

Dist. by Energique, Inc.
201 Apple Blvd.
Woodbine, IA 51579 800.869.8078

PACKAGE LABEL DISPLAY:

ENERGIQUE

SINCE 1987

PULSATILLA

200C

1 fl. oz. (30 ml)